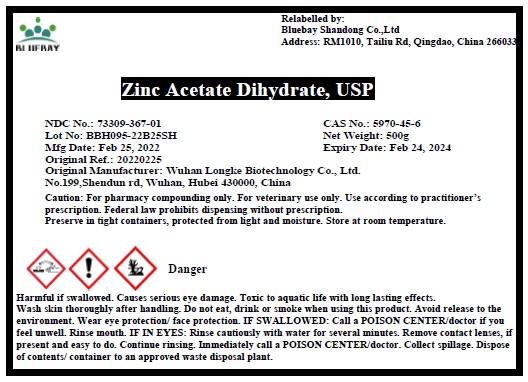 DRUG LABEL: Zinc Acetate Dihydrate
NDC: 73309-367 | Form: POWDER
Manufacturer: BLUEBAY SHANDONG CO.,LTD
Category: other | Type: BULK INGREDIENT - ANIMAL DRUG
Date: 20220311

ACTIVE INGREDIENTS: ZINC ACETATE 1 g/1 g

Zinc Acetate Dihydrate